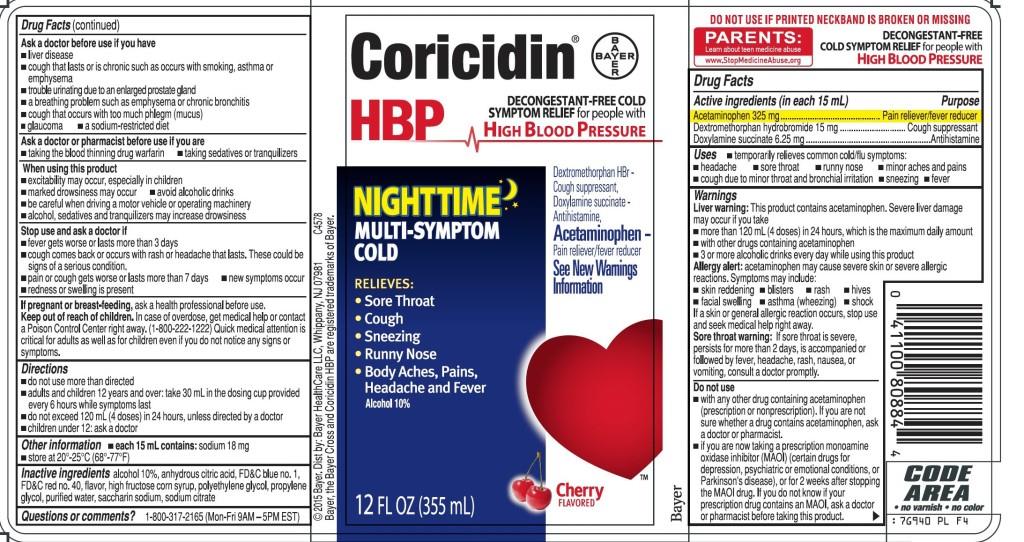 DRUG LABEL: Coricidin HBP Nighttime Multi-Symptom Cold
NDC: 11523-4358 | Form: LIQUID
Manufacturer: Bayer HealthCare LLC.
Category: otc | Type: HUMAN OTC DRUG LABEL
Date: 20251205

ACTIVE INGREDIENTS: DOXYLAMINE SUCCINATE 6.25 mg/15 mL; ACETAMINOPHEN 325 mg/15 mL; DEXTROMETHORPHAN HYDROBROMIDE 15 mg/15 mL
INACTIVE INGREDIENTS: ANHYDROUS CITRIC ACID; FD&C BLUE NO. 1; FD&C RED NO. 40; HIGH FRUCTOSE CORN SYRUP; POLYETHYLENE GLYCOL, UNSPECIFIED; PROPYLENE GLYCOL; WATER; SACCHARIN SODIUM

Coricidin HBP Nighttime Multi-Symptom Cold Liquid

Active ingredients (in each 15 mL)

Acetaminophen 325 mg | Pain reliever/fever reducer
Dextromethorphan hydrobromide 15 mg | Cough suppresant
Doxylamine succinate 6.25 mg | Antihistamine

Purpose

Acetaminophen 325 mg | Pain reliever/fever reducer
Dextromethorphan hydrobromide 15 mg | Cough suppresant
Doxylamine succinate 6.25 mg | Antihistamine

Uses

temporarily relieves common cold/flu symptoms:

- headache
- sore throat
- runny nose
- minor aches and pains
- cough due to minor throat and bronchial irritation
- sneezing
- fever

Warnings

Liver warning

This product contains acetaminophen. Severe liver damage may occur if you take

- more than 120 mL (4 doses) in 24 hours, which is the maximum daily amount
- with other drugs containing acetaminophen
- 3 or more alcoholic drinks every day while using this product

Allergy alert

acetaminophen may cause severe skin or severe allergic reactions. Symptoms may include:

- skin reddening
- blisters
- rash
- hives
- facial swelling
- asthma (wheezing)
- shock

If a skin or general allergic reaction occurs, stop use and seek medical help right away.

Sore throat warning

If sore throat is severe, persists for more than 2 days, is accompanied or followed by fever, headache, rash, nausea,or vomiting, consult a doctor promptly.

Do note use

- with any other products containing acetaminophen (prescription or nonprescription). If you are no sure whether a drug contains acetaminophen, ask a doctor or pharmacist.
- if you are now taking a prescription monoamine oxidase inhibitor (MAOI) (certain drugs for depression, psychiatric, or emotional conditions, or Parkinson's disease), or for 2 weeks after stopping the MAOI drug. If you do not know if your prescription drug contains an MAOI, ask a doctor or pharmacist before taking this product.

Ask a doctor before use if you have

- liver disease
- cough that lasts or is chronic such as occurs with smoking, asthma or emphysema
- trouble urinating due to an enlarged prostate gland
- a breathing problem such as emphysema or chronic bronchitis
- cough that occurs with too much phlegm (mucus)
- glaucoma
- a sodium-restricted diet

Ask a doctor or pharmacist before use if you are

- taking the blood thinning drug warfarin
- taking sedatives or tranquilizers

When using this product

- excitability may occur, especially in children
- marked drowsiness may occur
- avoid alcoholic drinks
- be careful when driving a motor vehicle or operating machinery
- alcohol, sedatives, and tranquilizers may increase drowsiness

Stop use and ask a doctor if

- fever gets worse or lasts more than 3 days
- cough comes back or occurs with rash or headache that lasts. These could be signs of a serious condition.
- pain, cough, or nasal congestion gets worse or lasts more than 7 days
- new symptoms occur
- redness or swelling is present

If pregnant or breast-feeding, ask a health professional before use.

Keep out of reach of children. In case of overdose, get medical help

or contact a Poison Control Center right away. (1-800-222-1222) Quick medical attention is critical for adults as well as for children even if you do not notice any signs or symptoms.

Directions

- do not take more than directed
- adults and children 12 years and over: take 30 mL in the dosing cup provided every 6 hours while symptoms last
- do not exceed 120 mL (4 doses) in 24 hours, unless directed by a doctor
- children under 12 years: ask a doctor

Other information

- each 15 mL contains: sodium 18 mg
- store at 20º-25ºC (68º-77ºF)

Inactive ingredients

alcohol 10%, anhydrous citric acid, FD&C blue no.1, FD&C red no.40, flavor, high fructose corn syrup, polyethylene glycol, propylene glycol, purified water, saccharin sodium, sodium citrate

Questions or comments? 1-800-317-2165 (Mon – Fri 9AM – 5PM EST)